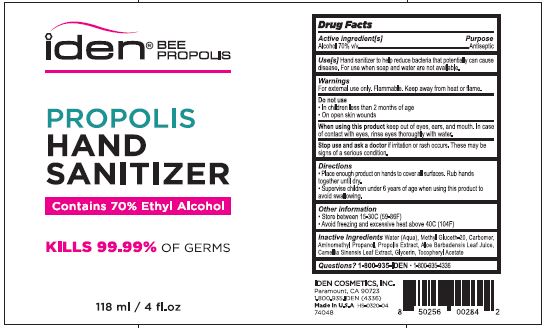 DRUG LABEL: PROPOLIS HAND SANITIZER
NDC: 74048-101 | Form: GEL
Manufacturer: Iden Cosmetics, Inc.
Category: otc | Type: HUMAN OTC DRUG LABEL
Date: 20200425

ACTIVE INGREDIENTS: ALCOHOL 70 mL/100 mL
INACTIVE INGREDIENTS: WATER; METHYL GLUCETH-20; CARBOMER COPOLYMER TYPE A (ALLYL PENTAERYTHRITOL CROSSLINKED); AMINOMETHYLPROPANOL; PROPOLIS WAX; ALOE VERA LEAF; GREEN TEA LEAF; GLYCERIN; .ALPHA.-TOCOPHEROL ACETATE

IDEN BEE PROPOLIS - PROPOLIS HAND SANITIZER

ACTIVE INGREDIENT

ALCOHOL 70% V/V

PURPOSE

ANTISEPTIC

USES

HAND SANITIZER TO HELP REDUCE BACTERIA THAT POTENTIALLY CAN CAUSE DISEASE. FOR USE WHEN SOAP AND WATER ARE NOT AVAILABLE.

WARNINGS

FOR EXTERNAL USE ONLY. FLAMMABLE, KEEP AWAY FROM HEAT OR FLAME.

DO NOT USE

- IN CHILDREN LESS THAN 2 MONTHS OF AGE
- ON OPEN SKIN WOUNDS

WHEN USING THIS PRODUCT KEEP OUT OF EYES, EARS, AND MOUTH. IN CASE OF CONTACT WITH EYES, RINSE EYES THOROUGHLY WITH WATER.

STOP USE AND ASK A DOCTOR IF IRRITATION OR OR RASH OCCURS. THESE MAY BE SIGNS OF A SERIOUS CONDITION.

KEEP OUT OF REACH OF CHILDREN.

IF SWALLOWED, GET MEDICAL HELP OR CONTACT A POISON CONTROL CENTER RIGHT AWAY.

DIRECTIONS

- PLACE ENOUGH PRODUCT ON HANDS TO COVER ALL SURFACES. RUB HANDS TOGETHER UNTIL DRY.
- SUPERVISE CHILDREN UNDER 6 YEARS OF AGE WHEN USING THIS PRODUCT TO AVOID SWALLOWING.

OTHER INFORMATION

- STORE BETWEEN 15-30C (59-86F)
- AVOID FREEZING AND EXCESSIVE HEAT ABOVE 40C (104F)

INACTIVE INGREDIENTS

WATER (AQUA), METHYL GLUCETH-20, CARBOMER, AMINOMETHYL PROPANOL, PROPOLIS EXTRACT, ALOE BARBADENSIS LEAF JUICE, CAMELLIA SINENSIS LEAF EXTRACT, GLYCERIN, TOCOPHERYL ACETATE

QUESTIONS?

1-800-935-IDEN * 1-800-935-4336